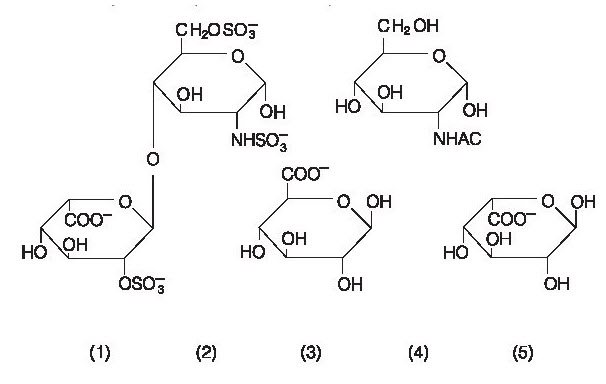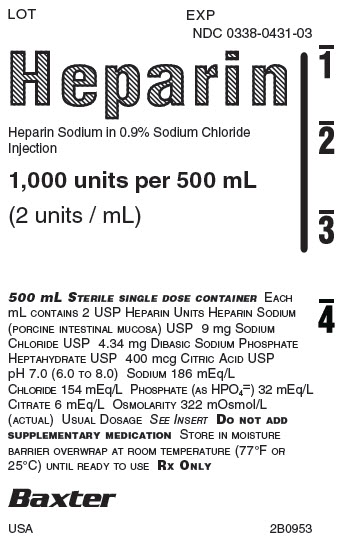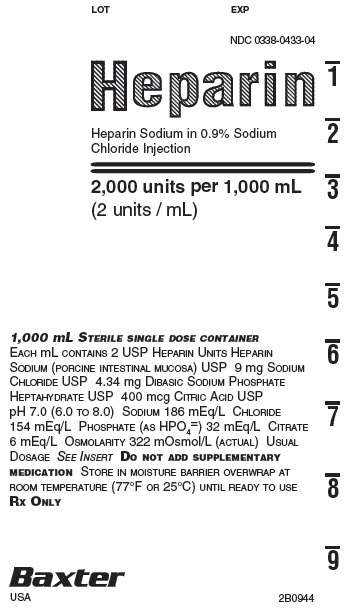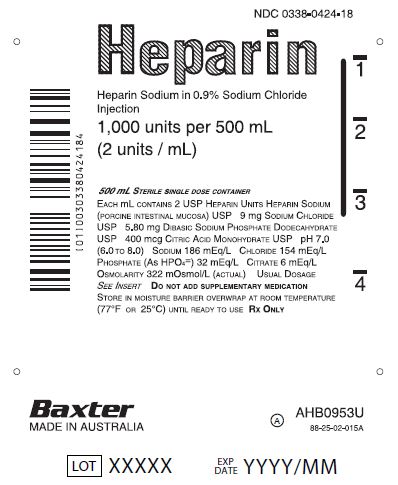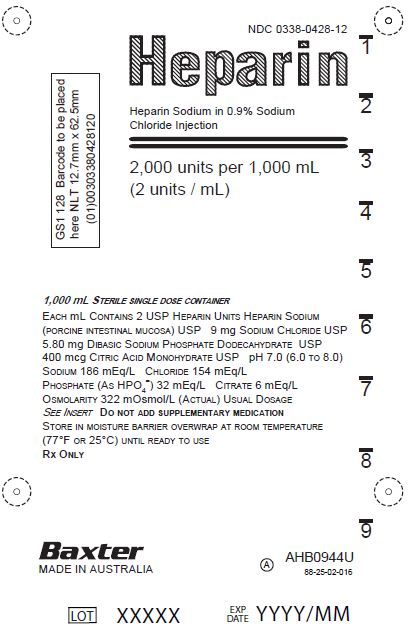 DRUG LABEL: HEPARIN SODIUM IN SODIUM CHLORIDE
NDC: 0338-0431 | Form: INJECTION, SOLUTION
Manufacturer: Baxter Healthcare Corporation
Category: prescription | Type: HUMAN PRESCRIPTION DRUG LABEL
Date: 20220103

ACTIVE INGREDIENTS: HEPARIN SODIUM 200 [USP'U]/100 mL
INACTIVE INGREDIENTS: SODIUM CHLORIDE 900 mg/100 mL; SODIUM PHOSPHATE, DIBASIC, HEPTAHYDRATE 434 mg/100 mL; CITRIC ACID MONOHYDRATE 40 mg/100 mL; WATER

HIGHLIGHTS OF PRESCRIBING INFORMATION

These highlights do not include all the information needed to use HEPARIN SODIUM IN SODIUM CHLORIDE INJECTION safely and effectively. See full prescribing information for HEPARIN SODIUM IN SODIUM CHLORIDE INJECTION.
HEPARIN SODIUM IN SODIUM CHLORIDE injection, for intravenous use
Initial U.S. Approval: 1939

RECENT MAJOR CHANGES

Dosage and Administration Preparation of Administration (2.1) 01/2022
Warnings and Precautions (5.2, 5.6, 5.7) 01/2022

1 INDICATIONS AND USAGE

Heparin Sodium in Sodium Chloride Injection at a concentration of 2 units/mL is indicated as an anticoagulant to maintain catheter patency. (1)

2 DOSAGE AND ADMINISTRATION

Infuse through intravenous catheter at a rate of 6 units per hour. (2.2)

3 DOSAGE FORMS AND STRENGTHS

- Injection: 1,000 USP units in Sodium Chloride in 500 mL single-dose infusion bag (2 USP units per mL) (3)
- Injection: 2,000 USP units in Sodium Chloride per 1,000 mL single-dose infusion bag (2 USP units per mL) (3)

4 CONTRAINDICATIONS

Heparin Sodium in Sodium Chloride Injection is contraindicated in patients with the following conditions: (4)

- With an uncontrollable active bleeding state, except when this is due to disseminated intravascular coagulation (5.1)
- With a history of heparin-induced thrombocytopenia (HIT) or heparin-induced thrombocytopenia with thrombosis (HITT) (5.2)
- With severe thrombocytopenia (5.2, 5.3)
- Known hypersensitivity to heparin or pork products (5.5)

5 WARNINGS AND PRECAUTIONS

- Hemorrhage: Fatal cases have occurred. Monitor for signs of bleeding and manage promptly. (5.1)
- HIT and HITT: Monitor for signs and symptoms and discontinue if indicative of HIT or HITT. (5.2)
- Hyperkalemia: Measure plasma potassium in patients at risk of hyperkalemia before starting heparin therapy and periodically in all patients. (5.6)
- Elevations of serum aminotransferases: Interpret elevation of these enzymes with caution. (5.7)

6 ADVERSE REACTIONS

Most common adverse reactions are: hemorrhage, thrombocytopenia, HIT and HITT, hypersensitivity, and elevations of aminotransferase levels. (6.1)

To report SUSPECTED ADVERSE REACTIONS, contact Baxter Healthcare at 1-866-888-2472 or FDA at 1-800-FDA-1088 or www.fda.gov/medwatch.

7 DRUG INTERACTIONS

Drugs that interfere with platelet aggregation or drugs that counteract coagulation may induce bleeding (7.2)

8 USE IN SPECIFIC POPULATIONS

Geriatric Use: A higher incidence of bleeding has been reported in patients over 60 years of age, especially women (5.7, 8.5)

FULL PRESCRIBING INFORMATION

1 INDICATIONS AND USAGE

Heparin Sodium in Sodium Chloride Injection at a concentration of 2 units/mL is indicated as an anticoagulant to maintain catheter patency.

2 DOSAGE AND ADMINISTRATION

2.1 Preparation for Administration

Do not administer unless solution is clear, and seal is intact. Parenteral drug products should be inspected visually for particulate matter and discoloration prior to administration whenever solution and container permit. Do not infuse this product under pressure.

To Open:

Tear overwrap down side at slit and remove solution container. Visually inspect the container. If the outlet port protector is damaged, detached, or not present, discard container as solution path sterility may be impaired. Some opacity of the plastic due to moisture absorption during the sterilization process may be observed. This is normal and does not affect the solution quality or safety. The opacity will diminish gradually. Check for minute leaks by squeezing inner bag firmly. If leaks are found discard solution as sterility may be impaired. Do not add supplementary medication.

Preparation for Administration:

1. Suspend container from eyelet support.
2. Remove plastic protector from outlet port at bottom of container.
3. Attach administration set. Refer to complete directions accompanying set.

All injections in VIAFLEX PLUS plastic containers are intended for administration using sterile equipment.

Single-dose container.

Discard any unused portion.

Do not reconnect partially used bags.

Because dosages of this drug are titrated to response, no additives should be made to Heparin Sodium in Sodium Chloride Injection.

Heparin sodium is not effective by oral administration and Heparin Sodium in Sodium Chloride Injection should not be given orally.

2.2 Maintenance of Catheter Patency

The recommended starting dose is 6 units per hour by intravenous infusion through an intravenous catheter to maintain catheter patency.

3 DOSAGE FORMS AND STRENGTHS

- Injection: 1,000 USP units per 500 mL (2 units per mL) clear solution in a single-dose infusion bag
- Injection: 2,000 USP units per 1,000 mL (2 units per mL) clear solution in a single-dose infusion bag

4 CONTRAINDICATIONS

The use of Heparin Sodium in Sodium Chloride Injection is contraindicated in patients with the following conditions:

- Uncontrollable active bleeding state, except when this is due to disseminated intravascular coagulation [see Warnings and Precautions (5.1)]
- History of heparin-induced thrombocytopenia (HIT) and heparin-induced thrombocytopenia with thrombosis (HITT) [see Warnings and Precautions (5.2)]
- Severe thrombocytopenia [see Warnings and Precautions (5.2, 5.3)]
- Known hypersensitivity to heparin or pork products (e.g., anaphylactoid reactions) [see Adverse Reactions (6.1)]

5 WARNINGS AND PRECAUTIONS

5.1 Hemorrhage

Avoid using heparin in the presence of major bleeding, except when the benefits of heparin therapy outweigh the potential risks.

Hemorrhage can occur at virtually any site in patients receiving heparin. Fatal hemorrhages have occurred. A higher incidence of bleeding has been reported in patients, particularly women, over 60 years of age [see Use in Specific Populations (8.5)]. An unexplained fall in hematocrit, fall in blood pressure, or any other unexplained symptom should lead to serious consideration of hemorrhagic event.

Use heparin sodium with caution in disease states in which there is increased risk of hemorrhage, including:

- Cardiovascular - Subacute bacterial endocarditis, severe hypertension.
- Surgical - During and immediately following (a) spinal tap or spinal anesthesia or (b) major surgery, especially involving the brain, spinal cord, or eye.
- Hematologic - Conditions associated with increased bleeding tendencies, such as hemophilia, thrombocytopenia, and some vascular purpuras.
- Gastrointestinal - Ulcerative lesions and continuous tube drainage of the stomach or small intestine.
- Patients with hereditary antithrombin III deficiency receiving concurrent antithrombin III therapy – The anticoagulant effect of heparin is enhanced by concurrent treatment with antithrombin III (human) in patients with hereditary antithrombin III deficiency. To reduce the risk of bleeding, reduce the heparin dose during concomitant treatment with antithrombin III (human).
- Other - Menstruation, liver disease with impaired hemostasis.

5.2 Heparin-Induced Thrombocytopenia and Heparin-Induced Thrombocytopenia with Thrombosis

Heparin-induced thrombocytopenia (HIT) is a serious immune-mediated reaction. HIT occurs in patients treated with heparin and is due to the development of antibodies to a platelet Factor 4-heparin complex that induce in vivo platelet aggregation. HIT may progress to the development of venous and arterial thromboses, a condition referred to as heparin-induced thrombocytopenia with thrombosis (HITT). Thrombotic events may also be the initial presentation for HITT. These serious thromboembolic events include deep vein thrombosis, pulmonary embolism, cerebral vein thrombosis, limb ischemia, stroke, myocardial infarction, mesenteric thrombosis, renal arterial thrombosis, skin necrosis, gangrene of the extremities that may lead to amputation, and possibly death.

Once HIT or HITT is diagnosed or strongly suspected, discontinue all heparin sources (including heparin flushes) and use an alternative anticoagulant.

Immune-mediated HIT is diagnosed based on clinical findings supplemented by laboratory tests confirming the presence of antibodies to heparin, or platelet activation induced by heparin. Obtain platelet counts at baseline and periodically during heparin administration. A drop in platelet count greater than 50% from baseline is considered indicative of HIT. Platelet counts begin to fall 5 to 10 days after exposure to heparin in heparin–naive individuals and reach a threshold by days 7 to 14. In contrast, “rapid onset” HIT can occur very quickly (within 24 hours following heparin initiation), especially in patients with a recent exposure to heparin (i.e., previous 3 months). Thrombosis development shortly after documenting thrombocytopenia is a characteristic finding in almost half of all patients with HIT.

Monitor any degree of thrombocytopenia closely. If the platelet count falls below 100,000/mm3 or if recurrent thrombosis develops, promptly discontinue heparin, evaluate for HIT and HITT, and, if necessary, administer an alternative anticoagulant. HIT or HITT can occur up to several weeks after the discontinuation of heparin therapy. Evaluate patients presenting with thrombocytopenia or thrombosis after discontinuation of heparin sodium for HIT or HITT.

5.3 Thrombocytopenia

Thrombocytopenia in patients receiving heparin has been reported at frequencies up to 30%. It can occur 2 to 20 days (average 5 to 9) following the onset of heparin therapy. Obtain platelet counts before and periodically during heparin therapy. Mild thrombocytopenia (count greater than 100,000/mm^3) may remain stable or reverse even if heparin is continued. However, monitor thrombocytopenia of any degree closely. If the count falls below 100,000/mm^3 or if recurrent thrombosis develops, promptly discontinue heparin, evaluate for HIT and HITT, and, if necessary, administer an alternative anticoagulant [see Warnings and Precautions (5.2)].

5.4 Heparin Resistance

Increased resistance to heparin is frequently encountered in fever, thrombosis, thrombophlebitis, infections with thrombosing tendencies, myocardial infarction, cancer, in postsurgical patients, and patients with anti-thrombin deficiency. Consider measurement of anti-thrombin levels if heparin resistance is suspected. Monitor coagulation tests frequently in such patients. It may be necessary to adjust the dose of heparin based on coagulation test monitoring, such as anti-Factor Xa levels and/or partial thromboplastin time.

5.5 Hypersensitivity

Hypersensitivity reactions with chills, fever and urticaria as the most usual manifestations and also asthma, rhinitis, lacrimation, and anaphylactoid reactions have been reported. Patients with documented hypersensitivity to heparin should be given the drug only in clearly life-threatening situations. Because Heparin Sodium in Sodium Chloride Injection is derived from animal tissue, it should be used with caution in patients with a history of allergy to pork products.

5.6 Hyperkalemia

Heparin can suppress adrenal secretion of aldosterone leading to hyperkalemia, particularly in patients with diabetes mellitus, chronic renal failure, pre-existing metabolic acidosis, a raised plasma potassium, or taking potassium sparing drugs. The risk of hyperkalemia appears to increase with duration of therapy but is usually reversible upon discontinuation of heparin.

Measure plasma potassium in patients at risk of hyperkalemia before starting heparin therapy and periodically in all patients treated for more than 5 days or earlier as deemed fit by the clinician.

5.7 Elevations of Serum Aminotransferases

Significant elevations of aspartate aminotransferase (AST) and alanine aminotransferase (ALT) levels have occurred patients who have received heparin. Elevation of these enzymes in patients receiving heparin should be interpreted with caution. These elevations typically resolve upon heparin discontinuation.

5.8 Laboratory Tests

Periodic platelet counts, hematocrits, and tests for occult blood in stool are recommended during the entire course of heparin therapy, regardless of the route of administration.

6 ADVERSE REACTIONS

The following clinically significant adverse reactions are described elsewhere in the labeling:

- Hemorrhage [see Warnings and Precautions (5.1)]
- Heparin-Induced Thrombocytopenia and Heparin-Induced Thrombocytopenia with Thrombosis [see Warnings and Precautions (5.2)]
- Thrombocytopenia [see Warnings and Precautions (5.3)]
- Heparin Resistance [see Warnings and Precautions (5.4)]
- Hypersensitivity [see Warnings and Precautions (5.5)]
- Hyperkalemia [see Warnings and Precautions (5.6)]
- Elevations of Serum Aminotransferases [see Warnings and Precautions (5.7)]

6.1 Postmarketing Experience

The following adverse reactions have been identified during post-approval use of heparin sodium. Because the reactions are reported voluntarily from a population of uncertain size, it is not always possible to reliably estimate their frequency.

Hemorrhage

Hemorrhage is the chief complication that may result from heparin therapy [see Warnings and Precautions (5.1)]. An overly prolonged clotting time or minor bleeding during therapy can usually be controlled by withdrawing the drug [see Overdosage (10)]. Gastrointestinal or urinary tract bleeding during anticoagulant therapy may indicate the presence of an underlying occult lesion. Bleeding can occur at any site but certain specific hemorrhagic complications may be difficult to detect:

- Adrenal hemorrhage, with resultant acute adrenal insufficiency, has occurred during anticoagulant therapy, including fatal cases.
- Ovarian (corpus luteum) hemorrhage developed in a number of women of reproductive age receiving short or long-term anticoagulant therapy.
- Retroperitoneal hemorrhage

Vascular Disorders: Contusion, Vasospastic reactions (including episodes of painful, ischemic, and cyanosed limbs).

HIT and HITT, including delayed onset cases, Thrombocytopenia [see Warnings and Precautions (5.2, 5.3)].

Histamine-like reactions: Such reactions have been observed at the site of injections. Necrosis of the skin has been reported at the site of subcutaneous injection of heparin, occasionally requiring skin grafting.

Hypersensitivity: General hypersensitivity reactions have been reported, with chills, fever, and urticaria as the most usual manifestations, and asthma, rhinitis, lacrimation, headache, nausea and vomiting, and anaphylactoid reactions, including shock, occurring more rarely. Itching and burning, especially on the plantar site of the feet, may occur [see Warnings and Precautions (5.5)].

Musculoskeletal, Connective Tissue and Bone Disorders: Osteoporosis with long-term administration of heparin.

Metabolism and Nutrition Disorders: Hyperkalemia.

General Disorders and Administration Site Conditions: Erythema, mild pain, ulceration.

Elevations of serum aminotransferases: Significant elevations of aspartate aminotransferase (AST) and alanine aminotransferase (ALT) levels have occurred patients who have received heparin.

Others: Cutaneous necrosis after systemic administration, delayed transient alopecia, priapism, and rebound hyperlipemia on discontinuation of heparin sodium have also been reported.

7 DRUG INTERACTIONS

7.1 Oral Anticoagulants

Heparin sodium may prolong the one-stage prothrombin time. Therefore, when heparin sodium is given with dicumarol or warfarin sodium, a period of at least 5 hours after the last intravenous dose or 24 hours after the last subcutaneous dose should elapse before blood is drawn if a valid prothrombin time is to be obtained.

7.2 Platelet Inhibitors

Drugs such as NSAIDS (including acetylsalicylic acid, ibuprofen, indomethacin, and celecoxib), dextran, phenylbutazone, thienopyridines, dipyridamole, hydroxychloroquine, glycoprotein IIv/IIa antagonists (including abciximab, eptifibatide, and tirofiban), and others that interfere with platelet-aggregation reactions (the main hemostatic defense of heparinized patients) may induce bleeding and should be used with caution in patients receiving heparin sodium. To reduce the risk of bleeding, a reduction in the dose of antiplatelet agent or heparin is recommended.

7.3 Other Medications that May Interfere with Heparin

Digitalis, tetracyclines, nicotine or antihistamines may partially counteract the anticoagulant action of heparin sodium. Intravenous nitroglycerin administered to heparinized patients may result in a decrease of the partial thromboplastin time with subsequent rebound effect upon discontinuation of nitroglycerin. Careful monitoring of partial thromboplastin time and adjustment of heparin dosage are recommended during coadministration of heparin and intravenous nitroglycerin.

Antithrombin III (human) – The anticoagulant effect of heparin is enhanced by concurrent treatment with antithrombin III (human) in patients with hereditary antithrombin III deficiency. To reduce the risk of bleeding, a reduced dosage of heparin is recommended during treatment with antithrombin III (human).

8 USE IN SPECIFIC POPULATIONS

8.1 Pregnancy

Risk Summary

There are no available data on Heparin Sodium in Sodium Chloride Injection use in pregnant women to inform a drug-associated risk of major birth defects and miscarriage. In published reports heparin exposure during pregnancy did not show evidence of an increased risk of adverse maternal or fetal outcomes in humans (see Data). Consider the benefits and risks of Heparin Sodium in Sodium Chloride Injection for the mother and possible risks to the fetus when prescribing Heparin Sodium in Sodium Chloride Injection to a pregnant woman.

The background risk of major birth defects and miscarriage for the indicated population is unknown. All pregnancies have a background risk of birth defect, loss, or other adverse outcomes. However, the background risk in the U.S. general population of major birth defects is 2 to 4% and of miscarriage is 15 to 20% of clinically recognized pregnancies.

Data

Human Data

The maternal and fetal outcomes associated with uses of heparin via various dosing methods and administration routes during pregnancy have been investigated in numerous studies. These studies generally reported normal deliveries with no maternal or fetal bleeding and no other complications.

Animal Data

In a published study conducted in rats and rabbits, pregnant animals received heparin intravenously during organogenesis at a dose of 10,000 units/kg/day, more than 50 times the maximum human daily dose based on body weight. The number of early resorptions increased in both species. There was no evidence of teratogenic effects.

8.2 Lactation

Risk Summary

There is no information regarding the presence of heparin in human milk, the effects on the breastfed child, or the effects on milk production. Due to its large molecular weight, heparin is not likely to be excreted in human milk.

The developmental and health benefits of breastfeeding should be considered along with the mother’s clinical need for heparin and any potential adverse effects on the breastfed child from heparin or from the underlying maternal condition.

8.4 Pediatric Use

Safety and effectiveness in pediatric patients have not been established.

8.5 Geriatric Use

A higher incidence of bleeding has been reported in patients over 60 years of age, especially women [see Warnings and Precautions (5.1)]. Clinical studies indicate that lower doses of heparin may be indicated in these patients [see Clinical Pharmacology (12.3)].

10 OVERDOSAGE

An overdose requires immediate medical attention and treatment. Bleeding is the chief sign of heparin overdosage. Easy bruising, petechial formations, nosebleeds, blood in urine or tarry stools may be the first signs or symptoms of a heparin overdose. In the event of symptomatic heparin overdose, consider stopping heparin infusion.

Neutralization of heparin effect:

When clinical circumstances (bleeding) require reversal of heparinization, protamine sulfate (1% solution) by slow infusion will neutralize heparin sodium. No more than 50 mg should be administered, very slowly in any 10-minute period. Each mg of protamine sulfate neutralizes approximately 100 USP heparin units. The amount of protamine required decreases over time as heparin is metabolized. Although the metabolism of heparin is complex, it may, for the purpose of choosing a protamine dose, be assumed to have a half-life of about 30 minutes after intravenous injection.

Ideally, the dose required to neutralize the action of heparin should be guided by blood coagulation tests or calculated from a protamine neutralization test.

Because fatal reactions often resembling anaphylaxis have been reported with protamine, it should be given only when resuscitation techniques and treatment of anaphylactoid shock are readily available.

For additional information consult the labeling of Protamine Sulfate Injection.

Blood or plasma transfusions may be necessary; these dilute but do not neutralize heparin.

11 DESCRIPTION

Heparin is a heterogenous group of straight-chain anionic mucopolysaccharides, called glycosaminoglycans having anticoagulant properties. Although others may be present, the main sugars occurring in heparin are: (1) α-L-iduronic acid 2-sulfate, (2) 2-deoxy-2-sulfamino-α-D-glucose 6-sulfate, (3) β-D-glucuronic acid, (4) 2-acetamido-2-deoxy-α-D- glucose, and (5) α-L-iduronic acid. These sugars are present in decreasing amounts, usually in the order (2) > (1) > (4) > (3) > (5), and are joined by glycosidic linkages, forming polymers of varying sizes. Heparin is strongly acidic because of its content of covalently linked sulfate and carboxylic acid groups. In heparin sodium, the acidic protons of the sulfate units are partially replaced by sodium ions.

Heparin Sodium in Sodium Chloride Injection is a buffered, sterile, nonpyrogenic solution of Heparin Sodium, USP derived from porcine intestinal mucosa, standardized for anticoagulant activity supplied in single dose containers for vascular administration. It contains no antimicrobial agents. The potency is determined by a biological assay using a USP reference standard based on units of heparin activity per milligram. Composition, osmolarity, pH and ionic concentration are shown in Table 1.

Table 1. Composition, Osmolarity, pH, and Ionic Concentration of Heparin in 0.9% Sodium Chloride Injection
Product Description and Size | 1,000 USP Heparin Units in 0.9% Sodium Chloride Injection, 500 mL | 1,000 USP Heparin Units in 0.9% Sodium Chloride Injection, 500 mL | 2,000 USP Heparin Units in 0.9% Sodium Chloride Injection, 1,000 mL | 2,000 USP Heparin Units in 0.9% Sodium Chloride Injection, 1,000 mL
NDC# | 0338-0431-03 | 0338-0424-18 | 0338-0433-04 | 0338-0428-12
Manufacturing Location | Jayuya, PR | Toongabbie, AUS | Jayuya, PR | Toongabbie, AUS
Heparin Sodium, USP (units/mL) | 2 | 2 | 2 | 2
Sodium Chloride, USP (NaCl) (g/L) | 9 | 9 | 9 | 9
Dibasic Sodium Phosphate Heptahydrate, USP (Na2HPO4*7H2O) (g/L) | 4.34 | ---- | 4.34 | ----
Dibasic Sodium Phosphate Dodecahydrate, USP (Na2HPO4*12H2O) (g/L) | ---- | 5.80 | ---- | 5.80
Citric Acid Hydrous, USP (C6H8O7*H2O) (g/L) | 0.4 | 0.4 | 0.4 | 0.4
Osmolarity [Normal physiologic osmolarity range is approximately 280 to 310 mOsmol/L. Administration of substantially hypertonic solutions (≥ 600 mOsmol/L) may cause vein damage.] (mOsmol/L) | 322 | 322 | 322 | 322
pH | 7.0 (6.0 to 8.0) | 7.0 (6.0 to 8.0) | 7.0 (6.0 to 8.0) | 7.0 (6.0 to 8.0)
Sodium (mEq/L) | 186 | 186 | 186 | 186
Chloride (mEq/L) | 154 | 154 | 154 | 154
Phosphate (as HPO4=) (mEq/L) | 32 (16 mmol/L) | 32 (16 mmol/L) | 32 (16 mmol/L) | 32 (16 mmol/L)
Citrate (mEq/L) | 6 | 6 | 6 | 6

This VIAFLEX PLUS plastic container is fabricated from a specially formulated polyvinyl chloride (PL 146 Plastic). VIAFLEX PLUS on the container indicates the presence of a drug additive in a drug vehicle. The VIAFLEX PLUS plastic container system utilizes the same container as the VIAFLEX plastic container system. The amount of water that can permeate from inside the container into the overwrap is insufficient to affect the solution significantly. Solutions in contact with the plastic container can leach out certain of its chemical components in very small amounts within the expiration period, e.g., di-2-ethylhexyl phthalate (DEHP), up to 5 parts per million. However, the safety of the plastic has been confirmed in tests in animals according to USP biological tests for plastic containers as well as by tissue culture toxicity studies.

12 CLINICAL PHARMACOLOGY

12.1 Mechanism of Action

Heparin interacts with the naturally occurring plasma protein, Antithrombin III, to induce a conformational change, which markedly enhances the serine protease activity of Antithrombin III, thereby inhibiting the activated coagulation factors involved in the closing sequence, particularly Xa and IIa. Small amounts of heparin inhibit Factor Xa, and larger amounts inhibit thrombin (Factor IIa). Heparin also prevents the formation of a stable fibrin clot by inhibiting the activation of the fibrin stabilizing factor. Heparin does not have fibrinolytic activity; therefore, it will not lyse existing clots.

12.2 Pharmacodynamics

Various times (activated clotting time, activated partial thromboplastin time, prothrombin time, whole blood clotting time) are prolonged by full therapeutic doses of heparin; in most cases, they are not measurably affected by low doses of heparin. Bleeding time is usually unaffected by heparin.

12.3 Pharmacokinetics

Absorption

Heparin is not absorbed through the gastrointestinal tract and therefore administered via parenteral route. Peak plasma concentration and the onset of action are achieved immediately after intravenous administration.

Distribution

Heparin is highly bound to antithrombin, fibrinogens, globulins, serum proteases and lipoproteins. The volume of distribution is 0.07 L/kg.

Elimination

Metabolism

Heparin does not undergo enzymatic degradation.

Excretion

Heparin is mainly cleared from the circulation by liver and reticuloendothelial cells mediated uptake into extravascular space. Heparin undergoes biphasic clearance, a) rapid saturable clearance (zero order process due to binding to proteins, endothelial cells and macrophages) and b) slower first order elimination. Low doses of heparin are cleared mostly by a saturable, rapid, zero-order process. Slower first order elimination usually occurs with very high doses of heparin and is dependent on renal function. The plasma half-life is dose-dependent, and it ranges from 0.5 to 2 h.

Specific Populations

Geriatric Patients

Patients over 60 years of age, following similar doses of heparin, may have higher plasma levels of heparin and longer activated partial thromboplastin times (APTTs) compared with patients under 60 years of age [see Use in Specific Populations (8.5)].

Renal and Hepatic Impairment

The rate of clearance of unfractionated heparin may be decreased in patients with renal or hepatic impairment. Patients with renal or hepatic impairment, following similar doses of heparin may have higher plasma levels of heparin compared with patient with normal renal and hepatic function [see Warnings and Precautions (5.1)].

13 NONCLINICAL TOXICOLOGY

13.1 Carcinogenesis, Mutagenesis, Impairment of Fertility

No long-term studies in animals have been performed to evaluate carcinogenic potential of heparin. Also, no reproduction studies in animals have been performed concerning mutagenesis or impairment of fertility.

16 HOW SUPPLIED/STORAGE AND HANDLING

Heparin Sodium in Sodium Chloride Injection in VIAFLEX PLUS plastic container is supplied as follows:

Product Description | Size | Code | NDC
1,000 USP Heparin Units in Sodium Chloride Injection | 500 mL | 2B0953 | 0338-0431-03
1,000 USP Heparin Units in Sodium Chloride Injection | 500 mL | AHB0953U | 0338-0424-18
2,000 USP Heparin Units in Sodium Chloride Injection | 1,000 mL | 2B0944 | 0338-0433-04
2,000 USP Heparin Units in Sodium Chloride Injection | 1,000 mL | AHB0944U | 0338-0428-12

Store at 25°C (77°F). Brief exposure up to 40°C (104°F) does not adversely affect the product. Avoid excessive heat.

17 PATIENT COUNSELING INFORMATION

Hemorrhage

Inform patients that it may take them longer than usual to stop bleeding, that they may bruise and/or bleed more easily when they are treated with heparin, and that they should report any unusual bleeding or bruising to their physician. Hemorrhage can occur at virtually any site in patients receiving heparin. Fatal hemorrhages have occurred [see Warnings and Precautions (5.1)].

Prior to Surgery

Advise patients to inform physicians and dentists that they are receiving heparin before any surgery is scheduled [see Warnings and Precautions (5.1)].

Heparin-Induced Thrombocytopenia

Inform patients of the risk of heparin-induced thrombocytopenia (HIT). HIT may progress to the development of venous and arterial thromboses, a condition known as heparin-induced thrombocytopenia with thrombosis (HITT). HIT and HITT can occur up to several weeks after the discontinuation of heparin therapy [see Warnings and Precautions (5.2)].

Hypersensitivity

Inform patients that generalized hypersensitivity reactions have been reported. Necrosis of the skin has been reported at the site of subcutaneous injection of heparin [see Warnings and Precautions (5.5), Adverse Reactions (6.1)].

Other Medications

Because of the risk of hemorrhage, advise patients to inform their physicians and dentists of all medications they are taking, including non-prescription medications, and before starting any new medication [see Drug Interactions (7.3)].

Manufactured by:
Baxter Healthcare Corporation
Deerfield, IL 60015 USA

Baxter, Viaflex and Viaflex Plus are trademarks of Baxter International Inc.

07-19-00-3508

ANZ881901209C

PACKAGE/LABEL PRINCIPAL DISPLAY PANEL

Container Label

Container Label

LOT EXP

NDC 0338-0431-03

Heparin
Heparin Sodium in 0.9% Sodium Chloride
Injection

1,000 units per 500 mL
(2 units/mL)

500 mL STERILE SINGLE DOSE CONTAINER EACH
mL CONTAINS 2 USP HEPARIN UNITS HEPARIN SODIUM
(PORCINE INTESTINAL MUCOSA) USP 9 mg SODIUM
CHLORIDE USP 4.34 mg DIBASIC SODIUM PHOSPHATE
HEPTAHYDRATE USP 400 mcg CITRIC ACID USP
pH 7.0 (6.0 TO 8.0) SODIUM 186 mEq/L
CHLORIDE 154 mEq/L PHOSPHATE (AS HPO4=) 32 mEq/L
CITRATE 6 mEq/L OSMOLARITY 322 mOsmol/L
(ACTUAL) USUAL DOSAGE SEE INSERT DO NOT ADD
SUPPLEMENTARY MEDICATION STORE IN MOISTURE
BARRIER OVERWRAP AT ROOM TEMPERATURE (77°F OR
25°C) UNTIL READY TO USE RX ONLY

Baxter Logo
USA 2B0953

1

2

Container Label

Container Label

LOT EXP

NDC 0338-0433-04

Heparin
Heparin Sodium in 0.9% Sodium
Chloride Injection

2,000 units per 1,000 mL
(2 units / mL)

1,000 mL STERILE SINGLE DOSE CONTAINER
EACH mL CONTAINS 2 USP HEPARIN UNITS HEPARIN
SODIUM (PORCINE INTESTINAL MUCOSA) USP 9 mg SODIUM
CHLORIDE USP 4.34 mg DIBASIC SODIUM PHOSPHATE
HEPTAHYDRATE USP 400 mcg CITRIC ACID USP
pH 7.0 (6.0 TO 8.0) SODIUM 186 mEq/L CHLORIDE
154 mEq/L PHOSPHATE (AS HPO4=) 32 mEq/L CITRATE
6 mEq/L OSMOLARITY 322 mOsmol/L (ACTUAL) USUAL
DOSAGE SEE INSERT DO NOT ADD SUPPLEMENTARY
MEDICATION STORE IN MOISTURE BARRIER OVERWRAP AT
ROOM TEMPERATURE (77°F OR 25°C) UNTIL READY TO USE
RX ONLY

Baxter Logo
USA 2B0944

07-25-58-614

1

2

3

4

5

6

7

8

9

Container Label

Container Label

NDC 0338-0424-18
Heparin

Heparin Sodium in 0.9% Sodium Chloride
Injection
1,000 units per 500 mL
(2 units / mL)

500 mL STERILE SINGLE DOSE CONTAINER
EACH mL CONTAINS 2 USP HEPARIN UNITS HEPARIN SODIUM
(PORCINE INTESTINAL MUCOSA) USP 9 mg SODIUM CHLORIDE
USP 5.80 mg DIBASIC SODIUM PHOSPHATE DODECAHYDRATE
USP 400 mcg CITRIC ACID MONOHYDRATE USP pH 7.0
(6.0 TO 8.0) SODIUM 186 mEq/L CHLORIDE 154 mEq/L
PHOSPHATE (AS HPO4=) 32 mEq/L CITRATE 6 mEq/L
OSMOLARITY 322 mOsmol/L (ACTUAL) USUAL DOSAGE
SEE INSERT DO NOT ADD SUPPLEMENTARY MEDICATION
STORE IN MOISTURE BARRIER OVERWRAP AT ROOM TEMPERATURE
(77°F OR 25°C) UNTIL READY TO USE RX ONLY

Baxter Logo
MADE IN AUSTRALIA

AHB0953U
A
88-25-02-015A

LOT XXXXX
EXP
DATE
YYYY/MM

1

2

3

4

Barcode
(01)00303380424184

Container Label

Container Label

NDC 0338-0428-12
Heparin

Heparin Sodium in 0.9% Sodium Chloride
Injection
2,000 units per 1,000 mL
(2 units / mL)

1,000 mL STERILE SINGLE DOSE CONTAINER
EACH mL CONTAINS 2 USP HEPARIN UNITS HEPARIN SODIUM
(PORCINE INTESTINAL MUCOSA) USP 9 mg SODIUM CHLORIDE USP
5.80 mg DIBASIC SODIUM PHOSPHATE DODECAHYDRATE USP
400 mcg CITRIC ACID MONOHYDRATE USP pH 7.0 (6.0 TO 8.0)
SODIUM 186 mEq/L CHLORIDE 154 mEq/L
PHOSPHATE (AS HPO4=) 32 mEq/L CITRATE 6 mEq/L
OSMOLARITY 322 mOsmol/L (ACTUAL) USUAL DOSAGE
SEE INSERT DO NOT ADD SUPPLEMENTARY MEDICATION
STORE IN MOISTURE BARRIER OVERWRAP AT ROOM TEMPERATURE
(77°F OR 25°C) UNTIL READY TO USE RX ONLY

Baxter Logo
MADE IN AUSTRALIA

AHB0944U
A
88-25-02-016

LOT XXXXX
EXP
DATE
YYYY/MM

1

2

3

4

5

6

7

8

9

GS1 128 Barcode to be placed
here NLT 12.7mm x 62.5mm
(01)00303380428120